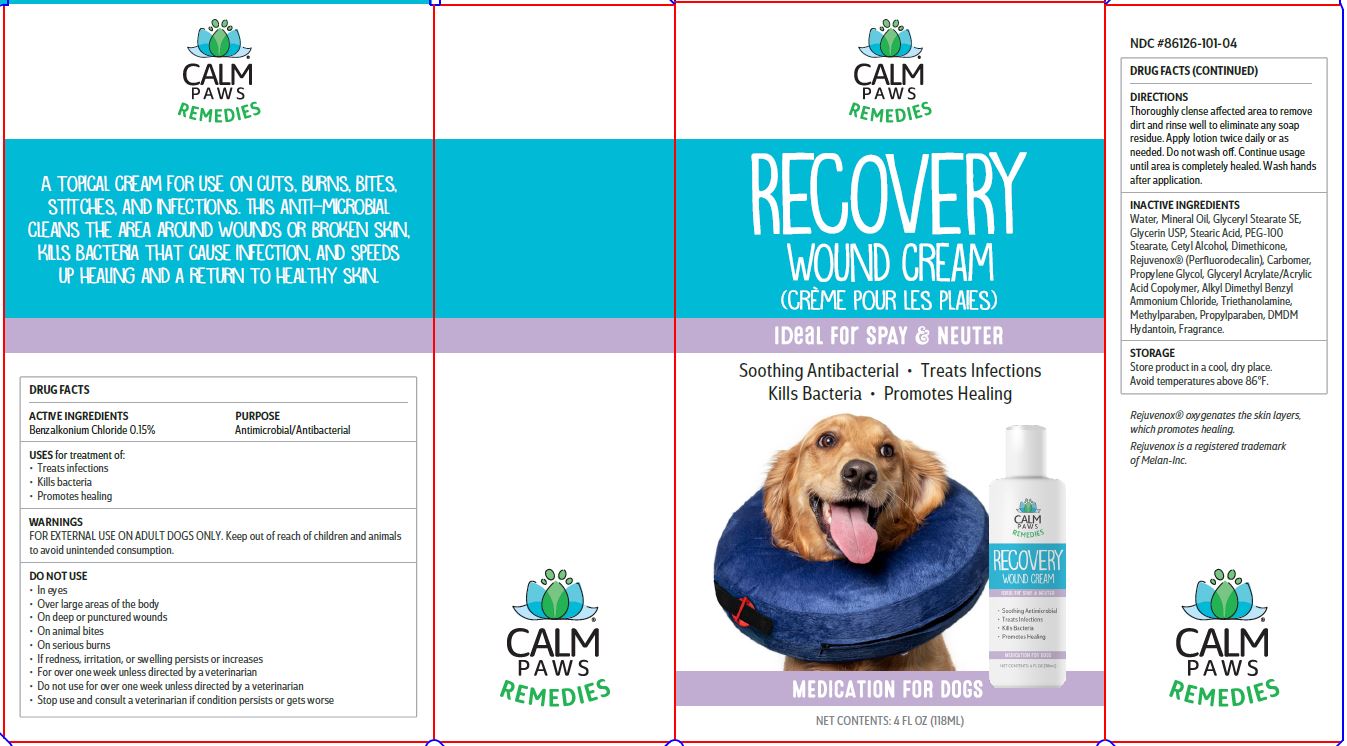 DRUG LABEL: RECOVERY WOUND
NDC: 86126-101 | Form: CREAM
Manufacturer: Acorn Pet Products, L.L.C.
Category: animal | Type: OTC ANIMAL DRUG LABEL
Date: 20221227

ACTIVE INGREDIENTS: BENZALKONIUM CHLORIDE 0.15 g/100 mL
INACTIVE INGREDIENTS: WATER; MINERAL OIL; GLYCERYL STEARATE SE; GLYCERIN; STEARIC ACID; PEG-100 STEARATE; CETYL ALCOHOL; DIMETHICONE; PERFLUNAFENE; CARBOMER HOMOPOLYMER, UNSPECIFIED TYPE; PROPYLENE GLYCOL; GLYCIDYL ACRYLATE; TROLAMINE; METHYLPARABEN; PROPYLPARABEN; DMDM HYDANTOIN

ACORN PET PRODUCTS - CALM PAWS REMEDIES RECOVERY WOUND CREAM (86126-101)

ACTIVE INGREDIENTS

BENZALKONIUM CHLORIDE 0.15%

USES

for treatment of:

- Treats infections
- Kills bacteria
- Promotes healing

WARNINGS

FOR EXTERNAL USE ON ADULT DOGS ONLY.
DO NOT USE

- In eyes
- Over large areas of the body
- On deep or punctured wounds
- On animal bites
- On serious burns
- If redness, irritation, or swelling persists or increases
- For over one week unless directed by a veterinarian
- Do not use for over one week unless directed by a veterinarian
- Stop use and consult a veterinarian if condition persists or gets worse

Keep out of reach of children and animals to avoid unintended consumption.

DIRECTIONS

Thoroughly clense affected area to remove dirt and rinse well to eliminate any soap residue. Apply lotion twice daily or as needed. Do not wash off. Continue usage until area is completely healed. Wash hands after application.

INACTIVE INGREDIENTS

Water, Mineral Oil, Glyceryl Stearate SE, Glycerin USP, Stearic Acid, PEG-100 Stearate, Cetyl Alcohol, Dimethicone, Rejuvenox® (Perfluorodecalin), Carbomer, Propylene Glycol, Glyceryl Acrylate/Acrylic Acid Copolymer, Alkyl Dimethyl Benzyl Ammonium Chloride, Triethanolamine, Methylparaben, Propylparaben, DMDM Hydantoin, Fragrance.

STORAGE

Store product in a cool, dry place.
Avoid temperatures above 86°F.